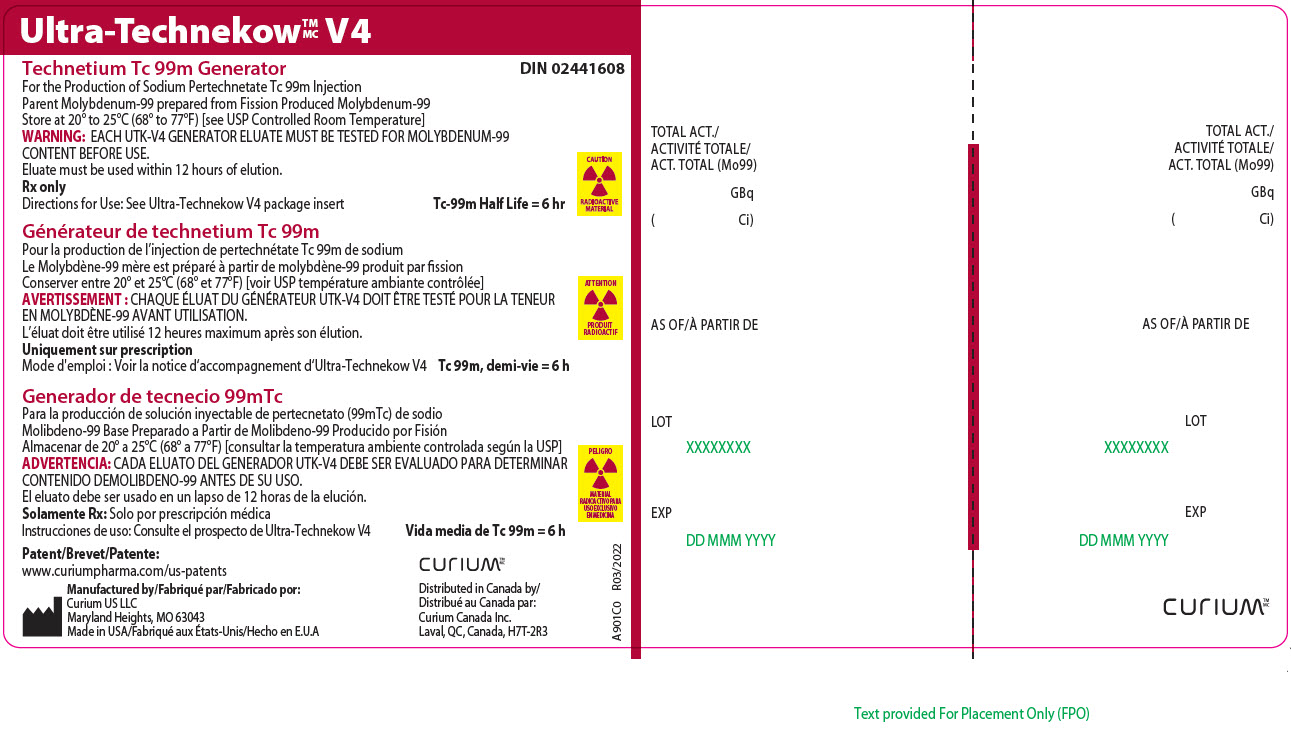 DRUG LABEL: Ultra-Technekow

NDC: 69945-010 | Form: INJECTION, SOLUTION
Manufacturer: Curium US LLC
Category: prescription | Type: HUMAN PRESCRIPTION DRUG LABEL
Date: 20241016

ACTIVE INGREDIENTS: TECHNETIUM TC-99M SODIUM PERTECHNETATE 1 Ci/1 1

Ultra-Technekow™V4
(Technetium Tc 99m Generator)
Rx only
For the Production of Sodium Pertechnetate Tc 99m Injection

DESCRIPTION

The Ultra-Technekow™V4 Generator is prepared with fission-produced molybdenum Mo-99 adsorbed onto alumina in a column shielded by lead, tungsten, or depleted uranium. The column assembly and shielding are encased in a plastic container that is covered with a plastic elution hood. The elution hood has an opening for the column assembly double inlet needles and an opening for the single outlet needle. The needles accommodate the sterile eluant vials that contain 0.9% Sodium Chloride Injection and sterile evacuated collection vials. A sterile vial containing a bacteriostat is supplied with the generator for the customer to aseptically seal the outlet needle after each elution.

This terminally sterilized generator provides a closed system for the production of sterile metastable technetium Tc-99m, which is produced by the decay of molybdenum Mo-99. Incorporated between the column outlet and the collection vial is a sterile 0.22 micrometer filter. Sterile, non-pyrogenic isotonic solutions of Sodium Pertechnetate Tc 99m Injection in 0.9% Sodium Chloride Injection can be obtained conveniently by periodic aseptic elution of the generator. These solutions should be clear, colorless, and free from any particulate matter. The Sodium Pertechnetate Tc 99m Injection is suitable for intravenous injection and direct instillation.

The carrier-free solution may be used as is, or diluted to the proper concentration. Over the life of the generator, an elution will contain an amount of technetium Tc-99m in direct proportion to the quantity of Mo-99 decay since the previous elution of the generator. The quantity of Tc-99m in the eluate is determined by quantity of Mo-99 on the column, and the elapsed time between elutions.

Each eluate of the generator should not contain more than the USP limit of 0.15 kilobecquerel molybdenum Mo-99 per megabecquerel technetium Tc-99m (0.15 microcurie Mo-99 per millicurie Tc-99m) per administered dose at the time of administration and an aluminum ion concentration of not more than 10 micrograms per milliliter of the generator eluate, both of which must be determined by the user before administration.

Since the eluate does not contain an antimicrobial agent, it should not be used after 12 hours from the time of generator elution.

Physical Characteristics

Technetium Tc-99m decays by isomeric transition with a physical half-life of 6 hours. The principal photon that is useful for detection and imaging studies is listed in Table 1.

Table 1. Principal Radiation Emission Data

Radiation | Mean Percent Per Disintegration | Energy (keV)
Gamma-2 | 89.07 | 140.5

External Radiation

The specific gamma ray constant for technetium Tc-99m is 0.795 R/hr-mCi at 1 cm. The first half-value layer is 0.023 cm of lead (Pb). A range of values for the relative attenuation of the radiation emitted by this radionuclide that results from interposition of various thicknesses of Pb is shown in Table 2. For example, the use of 0.27 cm thickness of Pb will attenuate the radiation emitted by a factor of about 1000.

Table 2. Radiation Attenuation by Lead Shielding

Shield Thickness (Pb) cm | Coefficient of Attenuation
0.023 | 0.5
0.09 | 10^-1
0.18 | 10^-2
0.27 | 10^-3

Molybdenum Mo-99 decays to technetium Tc-99m with a molybdenum Mo-99 half-life of 2.75 days, or 66 hours (see Table 3). The physical decay characteristics of molybdenum Mo-99 are such that only 88.6% of the decaying molybdenum Mo-99 atoms form technetium Tc-99m. Generator elutions may be made at any time, but the amount of technetium Tc-99m available will depend on the interval measured from the last elution. Approximately 47% of the maximum available technetium Tc-99m is reached after 6 hours and 95% after 23 hours. To correct for physical decay of molybdenum Mo-99 and technetium Tc-99m, the fractions that remain at selected intervals of time are shown in Tables 3 and 4.

Table 3. Physical Decay Chart; Molybdenum Mo-99, Half-Life 66 Hours

Days | Percent Remaining | Days | Percent Remaining
0 | 100 | 10 | 8
1 | 78 | 11 | 6
2 | 60 | 12 | 5
3 | 47 | 13 | 4
4 | 37 | 14 | 3
5 | 28 | 15 | 2
6 | 22 | 20 | 0.6
7 | 17 | 25 | 0.2
8 | 13 | 30 | 0.05
9 | 10

Table 4. Physical Decay Chart; Technetium Tc-99m, Half-Life 6 Hours

Hours | Percent Remaining | Hours | Percent Remaining
0* | 100 | 9 | 35
1 | 89 | 10 | 32
2 | 79 | 11 | 28
3 | 71 | 12 | 25
4 | 63 | 14 | 20
5 | 56 | 16 | 16
6 | 50 | 18 | 13
7 | 45 | 24 | 6
8 | 40

*Calibration Time

CLINICAL PHARMACOLOGY

The pertechnetate ion distributes in the body similarly to the iodide ion but is not organified when trapped in the thyroid gland. Pertechnetate concentrates in the thyroid gland, salivary glands, stomach and choroid plexus. After intravenous administration it gradually equilibrates with the extracellular space. A fraction is promptly excreted via the kidneys.

Following the administration of Sodium Pertechnetate Tc 99m as an eye drop, the drug mixes with tears within the conjunctival space. Within seconds to minutes it leaves the conjunctival space and escapes into the inferior meatus of the nose through the nasolacrimal drainage system. During this process the pertechnetate ion passes through the canaliculi, the lacrimal sac and the nasolacrimal duct. In the event of any anatomical or functional blockage of the drainage system there will be a backflow resulting in tearing (epiphora). Thus the pertechnetate escapes the conjunctival space in the tears.

While the major part of the pertechnetate escapes within a few minutes of normal drainage and tearing, it has been documented that there is some degree of transconjunctival absorption with turnover of 1.5% per minute in normal individuals, 2.1% per minute in patients without any sac and 2.7% per minute in patients with inflamed conjunctiva due to chronic dacryocystitis. Individual values may vary but these rates are probably representative and indicate that the maximum possible pertechnetate absorbed will remain below one thousandth of that used in other routine diagnostic procedures.

INDICATIONS AND USAGE

The Ultra-Technekow™ V4 generator is a source of sodium pertechnetate Tc 99m for use in the preparation of FDA-approved diagnostic radiopharmaceuticals, as described in the labeling of these diagnostic radiopharmaceutical kits.

Sodium Pertechnetate Tc 99m is used IN ADULTSas an agent for:

Thyroid Imaging
Salivary Gland Imaging
Urinary Bladder Imaging (direct isotopic cystography) for detection of vesico-ureteral reflux
Nasolacrimal Drainage System Imaging (dacryoscintigraphy)

Sodium Pertechnetate Tc 99m is used IN PEDIATRIC PATIENTSas an agent for:

Thyroid Imaging
Urinary Bladder Imaging (direct isotopic cystography) for the detection of vesico-ureteral reflux

CONTRAINDICATIONS

None.

WARNINGS

Radiation risks associated with the use of Sodium Pertechnetate Tc 99m are greater in pediatric patients than in adults and, in general, the younger the patient the greater the risk owing to greater absorbed radiation doses and longer life expectancy. These greater risks should be taken firmly into account in all benefit risk assessments involving pediatric patients.

Long-term cumulative radiation exposure may be associated with an increased risk of cancer.

Only use generator eluant specified for use with the Ultra-Technekow™V4 Generator. Do not use any other generator eluant or saline from any other source.

PRECAUTIONS

Radiopharmaceuticals should be used only by physicians who are qualified by training and experience in the safe use and handling of radionuclides and whose experience and training have been approved by the appropriate government agency authorized to license the use of radionuclides.

As in the use of any radioactive material, care should be taken to minimize radiation exposure to the patient consistent with proper patient management and to ensure minimum radiation exposure to occupational workers.

After the termination of the nasolacrimal imaging procedure, blowing the nose and washing the eyes with sterile distilled water or an isotonic sodium chloride solution will further minimize the radiation dose.

Since the eluate does not contain an antimicrobial agent, it should not be used after 12 hours from time of generator elution.

Carcinogenesis, Mutagenesis, Impairment of Fertility

No long-term animal studies have been performed to evaluate carcinogenic or mutagenic potential or whether Sodium Pertechnetate Tc 99m may affect fertility in males or females.

Pregnancy

In animal reproductive studies, Sodium Pertechnetate Tc 99m (as free pertechnetate) has been shown to cross the placental barrier. It is not known whether Sodium Pertechnetate Tc 99m can cause fetal harm when administered to a pregnant woman or can affect reproductive capacity.

Sodium Pertechnetate Tc 99m should be given to pregnant women only if the expected benefits to be gained clearly outweigh the potential hazards.

Ideally, examinations using radiopharmaceutical drug products - especially those elective in nature - of women of childbearing capability should be performed during the first ten days following the onset of menses.

Nursing Mothers

Technetium Tc-99m is excreted in human milk during lactation, therefore, formula-feedings should be substituted for breast-feedings.

Pediatric Use

See INDICATIONS AND USAGE and DOSAGE AND ADMINISTRATION sections. Also see the description of additional risk under WARNINGS.

ADVERSE REACTIONS

Allergic reactions including anaphylaxis have been reported infrequently following the administration of Sodium Pertechnetate Tc 99m.

DOSAGE AND ADMINISTRATION

Sodium Pertechnetate Tc 99m is administered by intravenous injection. When imaging the nasolacrimal drainage system, instill the Sodium Pertechnetate Tc 99m by the use of a device such as a micropipette or similar method which will ensure the accuracy of the dose.

For imaging the urinary bladder and ureters (direct isotopic cystography), the Sodium Pertechnetate Tc 99m is administered by direct instillation aseptically into the bladder via a urethral catheter, following which the catheter is flushed with approximately 200 mL of sterile saline directly into the bladder.

The suggested dose ranges employed for various diagnostic indications in the average ADULT PATIENT (70 kg) are as follows:

Vesico-ureteral imaging: 18.5 to 37 MBq (0.5 to 1 mCi)
Thyroid gland imaging: 37 to 370 MBq (1 to 10 mCi)
Salivary gland imaging: 37 to 185 MBq (1 to 5 mCi)
Nasolacrimal drainage system: Maximum dose of 3.7 MBq (100 µCi)

The recommended dosages in PEDIATRIC PATIENTS are:

Vesico-ureteral imaging: 18.5 to 37 MBq (0.5 to 1 mCi)
Thyroid gland imaging: 2.22 to 2.96 MBq (60 to 80 µCi) per kg body weight

The patient dose should be measured by a suitable radioactivity calibration system immediately prior to administration.

Parenteral drug products should be inspected visually for particulate matter and discoloration prior to administration whenever solution and container permit. If the solution is discolored, discontinue use of the generator immediately. The solution to be administered as the patient dose should be clear, colorless, and contain no particulate matter.

Radiation Dosimetry

The estimated absorbed radiation doses to an average ADULTand PEDIATRICpatient from an intravenous injection of various doses of Sodium Pertechnetate Tc 99m distributed uniformly in the total body are shown in Tables 5 and 6.

Table 5. Absorbed Radiation Doses from Intravenous Injection

Organ | Absorbed Radiation Dose (mGy) for a 1110 MBq (30mCi) dose
Adrenals | 4.1
Urinary Bladder Wall | 20
Bone Surfaces | 6.2
Brain | 2.2
Breasts | 2
Gallbladder Wall | 8.3
Stomach Wall | 29
Small Intestine | 18
ULI Wall | 63
LLI Wall | 23
Heart Wall | 3.5
Kidneys | 6
Liver | 4.7
Lungs | 2.9
Muscle | 3.6
Ovaries | 11
Pancreas | 6.3
Red Marrow | 4.1
Skin | 2
Spleen | 4.8
Testes | 3.1
Thymus | 2.7
Thyroid | 24
Uterus | 9
Remaining Tissues | 3.9
Effective Dose (mSv) | 14

To obtain radiation absorbed dose in rads (30 mCi dose) from the above table, divide individual organ values by a factor of 10 (does not apply for effective dose).

Table 6. Pediatric Absorbed Radiation Doses (mGy) from Intravenous Injection

Age | 15 years | 10 years | 5 years | 1 year
Administered activityin MBq (mCi) | 1110 (30) | 740 (20) | 555 (15) | 370 (10)
Organ
Adrenals | 5.3 | 5.4 | 6.2 | 7.1
Urinary Bladder Wall | 26 | 22 | 18 | 22
Bone Surfaces | 7.6 | 7.5 | 8.1 | 10
Brain | 2.8 | 3.1 | 3.7 | 4.5
Breasts | 2.6 | 2.6 | 3.2 | 4.1
Gallbladder Wall | 11 | 12 | 13 | 13
Stomach Wall | 38 | 36 | 43 | 59
Small Intestine | 22 | 23 | 26 | 30
ULI Wall | 81 | 89 | 110 | 140
LLI Wall | 31 | 33 | 40 | 48
Heart Wall | 4.5 | 4.6 | 5.2 | 6.4
Kidneys | 7.2 | 6.9 | 7.8 | 8.5
Liver | 6 | 6.7 | 8 | 9.1
Lungs | 3.8 | 3.8 | 4.4 | 5.3
Muscle | 4.5 | 4.5 | 5 | 6
Ovaries | 14 | 13 | 14 | 17
Pancreas | 8.1 | 8.2 | 8.9 | 10
Red Marrow | 5.1 | 5 | 5.2 | 6
Skin | 2.5 | 2.6 | 3.2 | 3.8
Spleen | 6 | 6 | 6.7 | 7.8
Testes | 4.1 | 4.3 | 4.9 | 6
Thymus | 3.6 | 3.5 | 4.2 | 5.3
Thyroid | 40 | 41 | 67 | 81
Uterus | 11 | 11 | 12 | 14
Remaining Tissues | 4.8 | 4.8 | 5.4 | 6.4
Effective Dose (mSv) | 19 | 19 | 23 | 29

To obtain radiation absorbed dose in rads (30 mCi dose) from the above table, divide individual organ values by a factor of 10 (does not apply for effective dose).

The estimated absorbed radiation doses to an ADULT patient from the nasolacrimal imaging procedure using a maximum dose of 3.7 megabecquerels (100 microcuries) of Sodium Pertechnetate Tc 99m are shown in Table 7.

Table 7. Absorbed Radiation Doses from Dacryoscintigraphy

Tissue | 3.7 MBq (100 µCi) Dose of Sodium Pertechnetate Tc 99m
Tissue | mGy | rad
Eye Lens:; If lacrimal fluid turnover is 16%/min | 0.140 | 0.014
If lacrimal fluid turnover is 100%/min | 0.022 | 0.002
If drainage system is blocked | 4.020 | 0.402
Total Body* | 0.011 | 0.001
Ovaries* | 0.030 | 0.003
Testes* | 0.009 | 0.001
Thyroid* | 0.130 | 0.013

*Assuming no blockage of draining system.

In pediatric patients, an average 30 minute exposure to 37 MBq (1 mCi) of Tc-99m pertechnetate following instillation for direct cystography, will result in the following estimated radiation doses:

Table 8. Absorbed Radiation Doses from Cystography (PEDIATRIC)

Age | Bladder wall dose, mGy (rad) | Gonadal dose, mGy (rad)
1 year | 3.6 (0.36) | 0.15 (0.015)
5 years | 2.0 (0.2) | 0.095 (0.0095)
10 years | 1.3 (0.13) | 0.066 (0.0066)
15 years | 0.92 (0.092) | 0.046 (0.0046)

HOW SUPPLIED

The Ultra-Technekow™V4 (Technetium Tc 99m) Generators contain the following amount of molybdenum Mo-99 at the date and time of calibration stated on the label.

Catalog No.

9010 37 gigabecquerels (1.0 curie)
NDC 69945-010-03

9015 55.5 gigabecquerels (1.5 curies)
NDC 69945-015-04

9020 74 gigabecquerels (2.0 curies)
NDC 69945-020-05

9025 92.5 gigabecquerels (2.5 curies)
NDC 69945-025-06

9030 111 gigabecquerels (3.0 curies)
NDC 69945-030-07

9035 129.5 gigabecquerels (3.5 curies)
NDC 69945-035-08

9051 185 gigabecquerels (5.0 curies)
NDC 69945-051-09

9060 222 gigabecquerels (6.0 curies)
NDC 69945-060-10

9075 277.5 gigabecquerels (7.5 curies)
NDC 69945-075-11

9110 407 gigabecquerels (11.0 curies)
NDC 69945-110-12

9140 518 gigabecquerels (14.0 curies)
NDC 69945-140-13

9160 592 gigabecquerels (16.0 curies)
NDC 69945-160-14

9190 703 gigabecquerels (19.0 curies)
NDC 69945-190-15

Each generator is supplied with the following components for the elution of the generator:

1 - Technestat™Vial, 5 mL, containing 0.5 mL of 1.5 mg/mL methylparaben and 0.2 mg/mL propylparaben, sterile, non-pyrogenic

1 - Package Insert

SUPPLIED SEPARATELY

30 - Evacuated Collecting Vials, 30 mL, sterile, non-pyrogenic, supplied with:

90 - Radioactive Materials Labels – Collection Vial (30 en, 30 fr, 30 es)

90 - Radioactive Materials Labels – Elution Shield (30 en, 30 fr, 30 es)

1 - Package Insert

30 - Generator Eluant, 0.9% Sodium Chloride Injection, sterile, non-pyrogenic, available in 5 mL, 10 mL, or 20 mL volumes, with 1 package insert. The eluant does not contain an antimicrobial agent. Each milliliter of Generator Eluant contains 9 milligrams of Sodium Chloride.

Storage

Store generator and Sodium Pertechnetate Tc 99m solution at controlled room temperature 20° to 25°C (68° to 77°F) [see USP Controlled Room Temperature].

Expiration Date

The generator should not be used after the expiration date stated on the label.

The expiration time of the Sodium Pertechnetate Tc 99m solution is not later than 12 hours after time of elution. If the eluate is used to reconstitute a kit, the radiolabeled kit should not be used after 12 hours from the time of generator elution or after the expiration time stated on the labeling for the prepared drug, whichever is earlier.

Directions for Use of the Technetium Tc 99m Generator

NOTE 1: Immediately upon delivery, the generator should be placed within a minimum of one-inch of lead shielding in such a manner
so as to minimize radiation exposure to attending personnel.

NOTE 2: Wear waterproof gloves during the elution procedure and during subsequent reconstitution of kits with the eluate.

NOTE 3: Use a shielded syringe to withdraw patient dose or to transfer Sodium Pertechnetate Tc 99m into mixing vials during kit
reconstitution.

NOTE 4: The needles in the generator are sterile beneath their covers, and the generator has been cleaned underneath the top cover.
Additional disinfection of these areas with agents containing alcohol may unfavorably influence the Tc-99m yield.

Eluting the generator every 24 hours will provide optimal amounts of Sodium Pertechnetate Tc 99m. However, the generator may be eluted whenever sufficient amounts of technetium Tc-99m have accumulated within the column.

For Example

Time After First Elution (hrs.) | Approximate Yield (% of First Elution)
1 | 10
2 | 19
3 | 27
4 | 35
5 | 41
6 | 47

Elution

1. Lift the generator by its handle and place it inside the auxiliary shield. Move the handle so that it is not covering the generator top by pushing it off to the side in between the generator and the auxiliary shield.
2. Remove and store the elution hood cover. Place the auxiliary shield top onto the top of the generator and align it with the elution hood.
3. Remove and store the tip cap plugs from the needles.
4. Remove the flip-top cap of the eluant vial; disinfect the stopper with a bacteriocide such as 70% isopropyl alcohol, allowing the stopper to dry before use. Invert the eluant vial and place stopper first into the saline vial alignment insert. Place the saline vial alignment insert and vial into the saline port of the auxiliary shield top and firmly push down the eluant vial until the stopper is punctured and seated at the base of the eluant needles.
5. Place the saline shield on top of the auxiliary shield top to cover the eluant vial.
6. Remove the flip-top cap of an evacuated vial; disinfect the stopper, allowing the stopper to dry before use. Place the evacuated vial into the elution tool.
7. Position the shielded evacuated vial by carefully lowering the elution tool into place on the elution needle. Piercing the septum of the evacuated vial with the elution needle will begin the elution process.
8. Wait until the evacuated vial has completely filled itself. This may take a few minutes. Never interrupt the elution by lifting the elution tool!
9. NOTE: Do not use generator eluate if its appearance is discolored, and discontinue use of the generator.
10. Remove the flip-top cap of the Technestat vial; disinfect the stopper, allowing the stopper to dry before use. Secure the Technestat vial into the Technestat vial holder.
11. Carefully remove the elution tool and replace with the shielded Technestat vial.
12. Determine the technetium Tc-99m concentration and molybdenum Mo-99 content for dispensing purposes. The generator eluate may be assayed using an appropriate detection system. The manufacturer’s instructions for operation of the instrument/equipment should be followed for measurement of Technetium Tc-99m and Molybdenum Mo-99 activity. NOTE: Molybdenum Mo-99 Breakthrough Limit- The acceptable limit is 0.15 kilobecquerel molybdenum Mo-99 per megabecquerel technetium Tc-99m (0.15 microcurie Mo-99 per millicurie Tc-99m) per administered dose in the Injection, at the time of administration (see USP, Sodium Pertechnetate Tc 99m Injection).
13. Determine the aluminum ion concentration of the eluate. NOTE: Aluminum Ion Breakthrough Limit- The acceptable limit is not more than 10 micrograms per milliliter of eluate (see USP, Sodium Pertechnetate Tc 99m Injection).

Subsequent Elutions

1. Remove the saline shield and then remove saline vial alignment insert from the saline port to remove the eluant vial from the eluant needles. Remove the vial from the saline vial alignment insert and reuse the saline vial alignment insert for subsequent elutions.
2. Remove the shielded Technestat vial by carefully lifting the Technestat vial shield from the elution needle.
3. Repeat steps 4 through 12 of the Elution procedure above.

Vacuum Loss

If the vacuum in the collecting vial is lost, do not attempt to re-evacuate the vial, but discard and use a new collecting vial.

Expired Generator Disposal

1. Following the life of the generator, remove and dispose of the used Technestat vial and the eluant vial.
2. Cover the elution and eluant needles with the stored tip cap plugs.
3. Place the stored elution hood cover onto the top of the generator.
4. The intact generator assembly should be either returned to Curium US LLC or disposed of in accordance with applicable regulations.

This generator may be received, used and administered only by authorized persons in designated clinical settings. Its receipt, storage, use, transfer and disposal are subject to the regulations and/or appropriate licenses of local competent official organizations.

©2022 Curium US LLC. Ultra-TechnekowTM, TechnestatTM, Curium™, and the Curium logo are trademarks of a Curium company.

Manufactured by:
Curium US LLC
Maryland Heights, MO 63043 USA
Made in USA

A901IS

Revised 5/2022

STERILE

CURIUM™

Principal Display Panel - 37 gigabecquerels

Ultra-TechnekowTM/MC V4
Technetium Tc 99m Generator DIN 02441608

For the Production of Sodium Pertechnetate Tc 99m Injection
Parent Molybdenum-99 prepared from Fission Produced Molybdenum-99
Store at 20º to 25ºC (68º to 77ºF) [see USP Controlled Room Temperature]
WARNING: EACH UTK-V4 GENERATOR ELUATE MUST BE TESTED FOR MOLYBDENUM-99 CONTENT BEFORE USE.
Eluate must be used within 12 hours of elution.
Rx onlyDirections for Use: See Ultra-Technekow V4 package insert Tc-99m Half Life = 6 hr

CAUTION
RADIOACTIVE MATERIAL

Patent/Brevet/Patente:www.curiumpharma.com/us-patents

Manufactured by/Fabriqué par/Fabricado por:Curium US LLC
Maryland Heights, MO 63043
Made in USA/Fabriqué aux États-Unis/Hecho en E.U.A

CURIUM TM/MC

Distributed in Canada by/
Distribué au Canada par:
Curium Canada Inc.
Laval, QC, Canada, H7T-2R3

A901C0
R03/2022

TOTAL ACT./
ACTIVITÉ TOTALE/
ACT. TOTAL (Mo99)
GBq
(Ci)

AS OF/À PARTIR DE

LOT

EXP

Principal Display Panel - 55.5 gigabecquerels

Ultra-TechnekowTM/MC V4
Technetium Tc 99m Generator DIN 02441608

For the Production of Sodium Pertechnetate Tc 99m Injection
Parent Molybdenum-99 prepared from Fission Produced Molybdenum-99
Store at 20º to 25ºC (68º to 77ºF) [see USP Controlled Room Temperature]
WARNING: EACH UTK-V4 GENERATOR ELUATE MUST BE TESTED FOR MOLYBDENUM-99 CONTENT BEFORE USE.
Eluate must be used within 12 hours of elution.
Rx onlyDirections for Use: See Ultra-Technekow V4 package insert Tc-99m Half Life = 6 hr

CAUTION
RADIOACTIVE MATERIAL

Patent/Brevet/Patente:www.curiumpharma.com/us-patents

Manufactured by/Fabriqué par/Fabricado por:Curium US LLC
Maryland Heights, MO 63043
Made in USA/Fabriqué aux États-Unis/Hecho en E.U.A

CURIUM TM/MC

Distributed in Canada by/
Distribué au Canada par:
Curium Canada Inc.
Laval, QC, Canada, H7T-2R3

A901C0
R03/2022

TOTAL ACT./
ACTIVITÉ TOTALE/
ACT. TOTAL (Mo99)
GBq
(Ci)

AS OF/À PARTIR DE

LOT

EXP

Principal Display Panel - 74 gigabecquerels

Ultra-TechnekowTM/MC V4
Technetium Tc 99m Generator DIN 02441608

For the Production of Sodium Pertechnetate Tc 99m Injection
Parent Molybdenum-99 prepared from Fission Produced Molybdenum-99
Store at 20º to 25ºC (68º to 77ºF) [see USP Controlled Room Temperature]
WARNING: EACH UTK-V4 GENERATOR ELUATE MUST BE TESTED FOR MOLYBDENUM-99 CONTENT BEFORE USE.
Eluate must be used within 12 hours of elution.
Rx onlyDirections for Use: See Ultra-Technekow V4 package insert Tc-99m Half Life = 6 hr

CAUTION
RADIOACTIVE MATERIAL

Patent/Brevet/Patente:www.curiumpharma.com/us-patents

Manufactured by/Fabriqué par/Fabricado por:Curium US LLC
Maryland Heights, MO 63043
Made in USA/Fabriqué aux États-Unis/Hecho en E.U.A

CURIUM TM/MC

Distributed in Canada by/
Distribué au Canada par:
Curium Canada Inc.
Laval, QC, Canada, H7T-2R3

A901C0
R03/2022

TOTAL ACT./
ACTIVITÉ TOTALE/
ACT. TOTAL (Mo99)
GBq
(Ci)

AS OF/À PARTIR DE

LOT

EXP

Principal Display Panel - 92.5 gigabecquerels

Ultra-TechnekowTM/MC V4
Technetium Tc 99m Generator DIN 02441608

For the Production of Sodium Pertechnetate Tc 99m Injection
Parent Molybdenum-99 prepared from Fission Produced Molybdenum-99
Store at 20º to 25ºC (68º to 77ºF) [see USP Controlled Room Temperature]
WARNING: EACH UTK-V4 GENERATOR ELUATE MUST BE TESTED FOR MOLYBDENUM-99 CONTENT BEFORE USE.
Eluate must be used within 12 hours of elution.
Rx onlyDirections for Use: See Ultra-Technekow V4 package insert Tc-99m Half Life = 6 hr

CAUTION
RADIOACTIVE MATERIAL

Patent/Brevet/Patente:www.curiumpharma.com/us-patents

Manufactured by/Fabriqué par/Fabricado por:Curium US LLC
Maryland Heights, MO 63043
Made in USA/Fabriqué aux États-Unis/Hecho en E.U.A

CURIUM TM/MC

Distributed in Canada by/
Distribué au Canada par:
Curium Canada Inc.
Laval, QC, Canada, H7T-2R3

A901C0
R03/2022

TOTAL ACT./
ACTIVITÉ TOTALE/
ACT. TOTAL (Mo99)
GBq
(Ci)

AS OF/À PARTIR DE

LOT

EXP

Principal Display Panel - 111 gigabecquerels

Ultra-TechnekowTM/MC V4
Technetium Tc 99m Generator DIN 02441608

For the Production of Sodium Pertechnetate Tc 99m Injection
Parent Molybdenum-99 prepared from Fission Produced Molybdenum-99
Store at 20º to 25ºC (68º to 77ºF) [see USP Controlled Room Temperature]
WARNING: EACH UTK-V4 GENERATOR ELUATE MUST BE TESTED FOR MOLYBDENUM-99 CONTENT BEFORE USE.
Eluate must be used within 12 hours of elution.
Rx onlyDirections for Use: See Ultra-Technekow V4 package insert Tc-99m Half Life = 6 hr

CAUTION
RADIOACTIVE MATERIAL

Patent/Brevet/Patente:www.curiumpharma.com/us-patents

Manufactured by/Fabriqué par/Fabricado por:Curium US LLC
Maryland Heights, MO 63043
Made in USA/Fabriqué aux États-Unis/Hecho en E.U.A

CURIUM TM/MC

Distributed in Canada by/
Distribué au Canada par:
Curium Canada Inc.
Laval, QC, Canada, H7T-2R3

A901C0
R03/2022

TOTAL ACT./
ACTIVITÉ TOTALE/
ACT. TOTAL (Mo99)
GBq
(Ci)

AS OF/À PARTIR DE

LOT

EXP

Principal Display Panel - 129.5 gigabecquerels

Ultra-TechnekowTM/MC V4
Technetium Tc 99m Generator DIN 02441608

For the Production of Sodium Pertechnetate Tc 99m Injection
Parent Molybdenum-99 prepared from Fission Produced Molybdenum-99
Store at 20º to 25ºC (68º to 77ºF) [see USP Controlled Room Temperature]
WARNING: EACH UTK-V4 GENERATOR ELUATE MUST BE TESTED FOR MOLYBDENUM-99 CONTENT BEFORE USE.
Eluate must be used within 12 hours of elution.
Rx onlyDirections for Use: See Ultra-Technekow V4 package insert Tc-99m Half Life = 6 hr

CAUTION
RADIOACTIVE MATERIAL

Patent/Brevet/Patente:www.curiumpharma.com/us-patents

Manufactured by/Fabriqué par/Fabricado por:Curium US LLC
Maryland Heights, MO 63043
Made in USA/Fabriqué aux États-Unis/Hecho en E.U.A

CURIUM TM/MC

Distributed in Canada by/
Distribué au Canada par:
Curium Canada Inc.
Laval, QC, Canada, H7T-2R3

A901C0
R03/2022

TOTAL ACT./
ACTIVITÉ TOTALE/
ACT. TOTAL (Mo99)
GBq
(Ci)

AS OF/À PARTIR DE

LOT

EXP

Principal Display Panel - 185 gigabecquerels

Ultra-TechnekowTM/MC V4
Technetium Tc 99m Generator DIN 02441608

For the Production of Sodium Pertechnetate Tc 99m Injection
Parent Molybdenum-99 prepared from Fission Produced Molybdenum-99
Store at 20º to 25ºC (68º to 77ºF) [see USP Controlled Room Temperature]
WARNING: EACH UTK-V4 GENERATOR ELUATE MUST BE TESTED FOR MOLYBDENUM-99 CONTENT BEFORE USE.
Eluate must be used within 12 hours of elution.
Rx onlyDirections for Use: See Ultra-Technekow V4 package insert Tc-99m Half Life = 6 hr

CAUTION
RADIOACTIVE MATERIAL

Patent/Brevet/Patente:www.curiumpharma.com/us-patents

Manufactured by/Fabriqué par/Fabricado por:Curium US LLC
Maryland Heights, MO 63043
Made in USA/Fabriqué aux États-Unis/Hecho en E.U.A

CURIUM TM/MC

Distributed in Canada by/
Distribué au Canada par:
Curium Canada Inc.
Laval, QC, Canada, H7T-2R3

A901C0
R03/2022

TOTAL ACT./
ACTIVITÉ TOTALE/
ACT. TOTAL (Mo99)
GBq
(Ci)

AS OF/À PARTIR DE

LOT

EXP

Principal Display Panel - 222 gigabecquerels

Ultra-TechnekowTM/MC V4
Technetium Tc 99m Generator DIN 02441608

For the Production of Sodium Pertechnetate Tc 99m Injection
Parent Molybdenum-99 prepared from Fission Produced Molybdenum-99
Store at 20º to 25ºC (68º to 77ºF) [see USP Controlled Room Temperature]
WARNING: EACH UTK-V4 GENERATOR ELUATE MUST BE TESTED FOR MOLYBDENUM-99 CONTENT BEFORE USE.
Eluate must be used within 12 hours of elution.
Rx onlyDirections for Use: See Ultra-Technekow V4 package insert Tc-99m Half Life = 6 hr

CAUTION
RADIOACTIVE MATERIAL

Patent/Brevet/Patente:www.curiumpharma.com/us-patents

Manufactured by/Fabriqué par/Fabricado por:Curium US LLC
Maryland Heights, MO 63043
Made in USA/Fabriqué aux États-Unis/Hecho en E.U.A

CURIUM TM/MC

Distributed in Canada by/
Distribué au Canada par:
Curium Canada Inc.
Laval, QC, Canada, H7T-2R3

A901C0
R03/2022

TOTAL ACT./
ACTIVITÉ TOTALE/
ACT. TOTAL (Mo99)
GBq
(Ci)

AS OF/À PARTIR DE

LOT

EXP

Principal Display Panel - 277.5 gigabecquerels

Ultra-TechnekowTM/MC V4
Technetium Tc 99m Generator DIN 02441608

For the Production of Sodium Pertechnetate Tc 99m Injection
Parent Molybdenum-99 prepared from Fission Produced Molybdenum-99
Store at 20º to 25ºC (68º to 77ºF) [see USP Controlled Room Temperature]
WARNING: EACH UTK-V4 GENERATOR ELUATE MUST BE TESTED FOR MOLYBDENUM-99 CONTENT BEFORE USE.
Eluate must be used within 12 hours of elution.
Rx onlyDirections for Use: See Ultra-Technekow V4 package insert Tc-99m Half Life = 6 hr

CAUTION
RADIOACTIVE MATERIAL

Patent/Brevet/Patente:www.curiumpharma.com/us-patents

Manufactured by/Fabriqué par/Fabricado por:Curium US LLC
Maryland Heights, MO 63043
Made in USA/Fabriqué aux États-Unis/Hecho en E.U.A

CURIUM TM/MC

Distributed in Canada by/
Distribué au Canada par:
Curium Canada Inc.
Laval, QC, Canada, H7T-2R3

A901C0
R03/2022

TOTAL ACT./
ACTIVITÉ TOTALE/
ACT. TOTAL (Mo99)
GBq
(Ci)

AS OF/À PARTIR DE

LOT

EXP

Principal Display Panel - 407 gigabecquerels

Ultra-TechnekowTM/MC V4
Technetium Tc 99m Generator DIN 02441608

For the Production of Sodium Pertechnetate Tc 99m Injection
Parent Molybdenum-99 prepared from Fission Produced Molybdenum-99
Store at 20º to 25ºC (68º to 77ºF) [see USP Controlled Room Temperature]
WARNING: EACH UTK-V4 GENERATOR ELUATE MUST BE TESTED FOR MOLYBDENUM-99 CONTENT BEFORE USE.
Eluate must be used within 12 hours of elution.
Rx onlyDirections for Use: See Ultra-Technekow V4 package insert Tc-99m Half Life = 6 hr

CAUTION
RADIOACTIVE MATERIAL

Patent/Brevet/Patente:www.curiumpharma.com/us-patents

Manufactured by/Fabriqué par/Fabricado por:Curium US LLC
Maryland Heights, MO 63043
Made in USA/Fabriqué aux États-Unis/Hecho en E.U.A

CURIUM TM/MC

Distributed in Canada by/
Distribué au Canada par:
Curium Canada Inc.
Laval, QC, Canada, H7T-2R3

A901C0
R03/2022

TOTAL ACT./
ACTIVITÉ TOTALE/
ACT. TOTAL (Mo99)
GBq
(Ci)

AS OF/À PARTIR DE

LOT

EXP

Principal Display Panel - 518 gigabecquerels

Ultra-TechnekowTM/MC V4
Technetium Tc 99m Generator DIN 02441608

For the Production of Sodium Pertechnetate Tc 99m Injection
Parent Molybdenum-99 prepared from Fission Produced Molybdenum-99
Store at 20º to 25ºC (68º to 77ºF) [see USP Controlled Room Temperature]
WARNING: EACH UTK-V4 GENERATOR ELUATE MUST BE TESTED FOR MOLYBDENUM-99 CONTENT BEFORE USE.
Eluate must be used within 12 hours of elution.
Rx onlyDirections for Use: See Ultra-Technekow V4 package insert Tc-99m Half Life = 6 hr

CAUTION
RADIOACTIVE MATERIAL

Patent/Brevet/Patente:www.curiumpharma.com/us-patents

Manufactured by/Fabriqué par/Fabricado por:Curium US LLC
Maryland Heights, MO 63043
Made in USA/Fabriqué aux États-Unis/Hecho en E.U.A

CURIUM TM/MC

Distributed in Canada by/
Distribué au Canada par:
Curium Canada Inc.
Laval, QC, Canada, H7T-2R3

A901C0
R03/2022

TOTAL ACT./
ACTIVITÉ TOTALE/
ACT. TOTAL (Mo99)
GBq
(Ci)

AS OF/À PARTIR DE

LOT

EXP

Principal Display Panel - 592 gigabecquerels

Ultra-TechnekowTM/MC V4
Technetium Tc 99m Generator DIN 02441608

For oduction of Sodium Pertechnetate Tc 99m Injection
Parent Molybdenum-99 prepared from Fission Produced Molybdenum-99
Store at 20º to 25ºC (68º to 77ºF) [see USP Controlled Room Temperature]
WARNING: EACH UTK-V4 GENERATOR ELUATE MUST BE TESTED FOR MOLYBDENUM-99 CONTENT BEFORE USE.
Eluate must be used within 12 hours of elution.
Rx onlyDirections for Use: See Ultra-Technekow V4 package insert Tc-99m Half Life = 6 hr

CAUTION
RADIOACTIVE MATERIAL

Patent/Brevet/Patente:www.curiumpharma.com/us-patents

Manufactured by/Fabriqué par/Fabricado por:Curium US LLC
Maryland Heights, MO 63043
Made in USA/Fabriqué aux États-Unis/Hecho en E.U.A

CURIUM TM/MC

Distributed in Canada by/
Distribué au Canada par:
Curium Canada Inc.
Laval, QC, Canada, H7T-2R3

A901C0
R03/2022

TOTAL ACT./
ACTIVITÉ TOTALE/
ACT. TOTAL (Mo99)
GBq
(Ci)

AS OF/À PARTIR DE

LOT

EXP

Principal Display Panel - 703 gigabecquerels

Ultra-TechnekowTM/MC V4
Technetium Tc 99m Generator DIN 02441608

For the Production of Sodium Pertechnetate Tc 99m Injection
Parent Molybdenum-99 prepared from Fission Produced Molybdenum-99
Store at 20º to 25ºC (68º to 77ºF) [see USP Controlled Room Temperature]
WARNING: EACH UTK-V4 GENERATOR ELUATE MUST BE TESTED FOR MOLYBDENUM-99 CONTENT BEFORE USE.
Eluate must be used within 12 hours of elution.
Rx onlyDirections for Use: See Ultra-Technekow V4 package insert Tc-99m Half Life = 6 hr

CAUTION
RADIOACTIVE MATERIAL

Patent/Brevet/Patente:www.curiumpharma.com/us-patents

Manufactured by/Fabriqué par/Fabricado por:Curium US LLC
Maryland Heights, MO 63043
Made in USA/Fabriqué aux États-Unis/Hecho en E.U.A

CURIUM TM/MC

Distributed in Canada by/
Distribué au Canada par:
Curium Canada Inc.
Laval, QC, Canada, H7T-2R3

A901C0
R03/2022

TOTAL ACT./
ACTIVITÉ TOTALE/
ACT. TOTAL (Mo99)
GBq
(Ci)

AS OF/À PARTIR DE

LOT

EXP